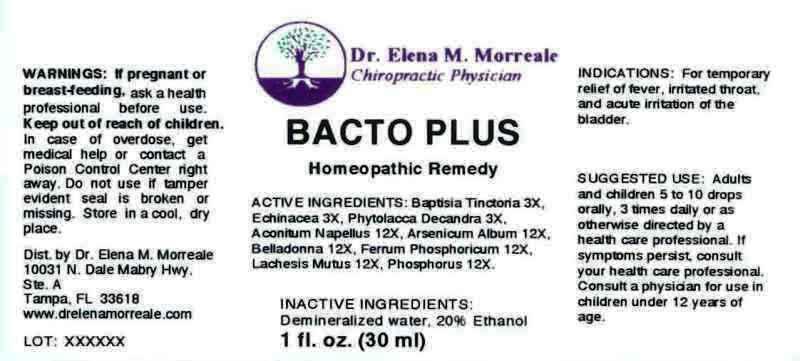 DRUG LABEL: Bacto Plus
NDC: 50813-0001 | Form: LIQUID
Manufacturer: Dr. Elena M. Morreale, Chiropractic Life Center
Category: homeopathic | Type: HUMAN OTC DRUG LABEL
Date: 20131010

ACTIVE INGREDIENTS: BAPTISIA TINCTORIA 3 [hp_X]/1 mL; ECHINACEA, UNSPECIFIED 3 [hp_X]/1 mL; PHYTOLACCA AMERICANA ROOT 3 [hp_X]/1 mL; ACONITUM NAPELLUS 12 [hp_X]/1 mL; ARSENIC TRIOXIDE 12 [hp_X]/1 mL; ATROPA BELLADONNA 12 [hp_X]/1 mL; FERRUM PHOSPHORICUM 12 [hp_X]/1 mL; LACHESIS MUTA VENOM 12 [hp_X]/1 mL; PHOSPHORUS 12 [hp_X]/1 mL
INACTIVE INGREDIENTS: WATER; ALCOHOL

DRUG FACTS:

ACTIVE INGREDIENTS:

Baptisia Tinctoria 3X, Echinacea 3X, Phytolacca Decandra 3X, Aconitum Napellus 12X, Arsenicum Album 12X, Belladonna 12X, Ferrum Phosphoricum 12X, Lachesis Mutus 12X, Phosphorus 12X.

INDICATIONS:

For temporary relief of fever, irritated throat, and acute irritation of the bladder.

WARNINGS:

If pregnant or breast-feeding, ask a health professional before use.

Keep out of reach of children. In case of overdose, get medical help or contact a Poison Control Center right away.

Do not use if tamper evident seal is broken or missing.

Store in a cool, dry place.

Keep out of reach of children. In case of overdose, get medical help or contact a Poison Control Center right away.

DIRECTIONS:

Adults and children 5 to 10 drops orally, 3 times daily or as otherwise directed by a health care professional. If symptoms persist, contsult your health care professional. Consult a physician for use in children under 12 years of age.

INDICATIONS:

For temporary relief of fever, irritated throat, and acute irritation of the bladder.

INACTIVE INGREDIENTS:

Demineralized Water, 20% Ethanol

QUESTIONS:

Dist. by Dr. Elena M. Morreale

10031 N. Dale Mabry Hwy, Ste. A

Tampa, FL 33618

www.drelenamorreale.com

PACKAGE DISPLAY LABEL:

Dr. Elena M. Morreale

Chiropractic Physician

BACTO PLUS

Homeopathic Remedy

1 fl. oz. (30 ml)